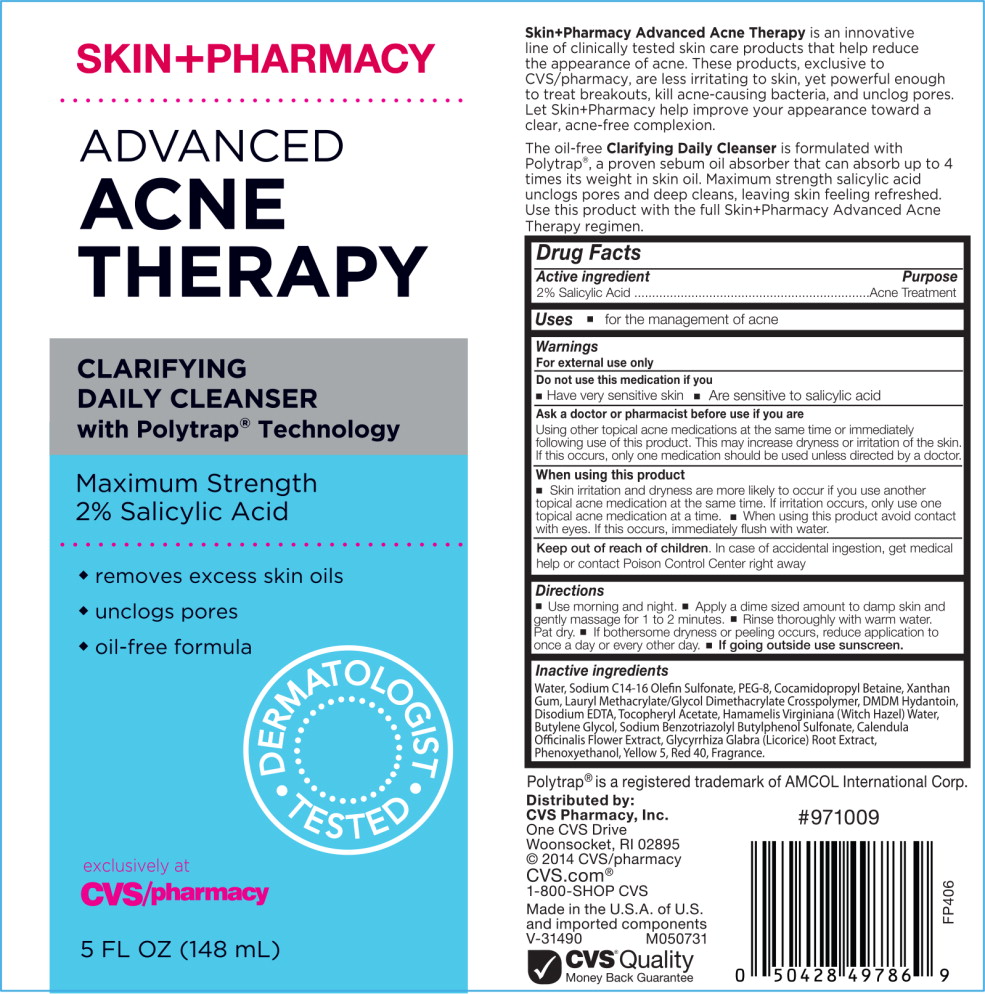 DRUG LABEL: SKIN PHARMACY ADVANCED ACNE THERAPY CLARIFYING DAILY CLEANSER
NDC: 68634-064 | Form: LIQUID
Manufacturer: AMCOL Health & Beauty Solutions, Inc. DBA
Category: otc | Type: HUMAN OTC DRUG LABEL
Date: 20160913

ACTIVE INGREDIENTS: salicylic acid 20 g/2 mL
INACTIVE INGREDIENTS: Water; sodium C14-16 olefin sulfonate; polyethylene glycol 4000; cocamidopropyl betaine; Xanthan gum; DMDM Hydantoin; edetate disodium; .alpha.-tocopherol acetate, DL-; Hamamelis virginiana flower water; Butylene glycol; Calendula Officinalis flower; licorice; Phenoxyethanol; FD&C Yellow No. 5; FD&C red no. 40; Lauryl Methacrylate/Glycol Dimethacrylate Crosspolymer

SKIN+PHARMACY
ADVANCED ACNE THERAPY
CLARIFYING DAILY CLEANSER

HBS Code (Labeler): FP40604-5.1

Distributor: CVS Pharmacy, Inc.

Human OTC Drug

Active Ingredients: Salicylic Acid 2%

LABEL TEXT

________________________________________________________

SKIN+PHARMACY

ADVANCED ACNE THERAPY

CLARIFYING DAILY CLEANSER with Polytrap® Technology

Maximum Strength 2% Salicylic Acid

- removes excess skin oils
- unclogs pores
- oil-free formula

DERMATOLOGIST TESTED

exclusively at CVS/pharmacy

5 FL OZ (148 mL)

Skin+Pharmacy Advanced Acne Therapy is an innovative line of clinically tested skin care products that help reduce the appearance of acne. These products, exclusive to CVS/pharmacy, are less irritating to skin, yet powerful enough to treat breakouts, kill acne-causing bacteria, and unclog pores. Let Skin+Pharmacy help improve your appearance toward a clear, acne-free complexion.

The oil-free Clarifying Daily Cleanser is formulated with Polytrap®, a proven sebum oil absorber that can absorb up to 4 times its weight in skin oil. Maximum strength salicylic acid unclogs pores and deep cleans, leaving skin feeling refreshed. Use this product with the full Skin+Pharmacy Advanced Acne Therapy regimen.

Drug Facts

Active Ingredient

2% Salicylic Acid

Purpose

Acne

INDICATIONS AND USAGE

Uses for the management of acne

Warnings

For external use only

Do not use this medication if you

- Have very sensitive skin
- Are sensitive to salicylic acid

Ask a doctor or pharmacist before use if you are

Using other topical acne medications at the same time or immediately following use of this product. This may increase dryness or irritation of the skin. If this occurs, only one medication should be used unless directed by a doctor.

When using this product

- Skin irritation and dryness are more likely to occur if you use another topical acne medication at the same time. If irritation occurs, only use one topical acne medication at the same time.
- When using this product avoid contact with eyes. If this occurs, immediately flush with water.

Keep out of reach of children. In case of accidental ingestion, get medical help or contact Poison Control Center right away.

Directions

- Use morning and night.
- Apply a dime sized amount to damp skin and gently massage for 1 to 2 minutes.
- Rinse thoroughly with warm water. Pat dry.
- If bothersome dryness or peeling occurs, reduce application to once a day or every other day.
- If going outside use sunscreen.

Inactive ingredients

Water, Sodium C14-16 Olefin Sulfonate, PEG-8, Cocamidopropyl Betaine, Xanthan Gum, Lauryl Methacrylate/Glycol Dimethacrylate Crosspolymer, DMDM Hydantoin, Disodium EDTA, Tocopheryl Acetate, Hamamelis Virginiana (Witch Hazel) Water, Butylene Glycol, Sodium Benzotriazolyl Butylphenol Sulfonate, Calendula Officinalis Flower Extract, Glycyrrhiza Glabra (Licorice) Root Extract, Phenoxyethanol, Yellow 5, Red 40, Fragrance.

Polytrap® is a registered trademark of AMCOL International Corp.

Save carton for complete labeling since all warnings are not included on the inner package.

Distributed by: CVS Pharmacy, Inc.

One CVS Drive, Woonsocket, RI 02895

© 2014 CVS/pharmacy

CVS.com® 1-800-SHOP CVS

Made in the U.S.A. of U.S. and imported components

V-31490

M050731

CVS® Quality

Money Back Guarantee

#971009

FP406

________________________________________________________

end of text

160913

AMCOL Health & Beauty Solutions, Inc. DBA AMCOL Household and Personal Care

301 Laser Lane Lafayette, LA 70507 | www.amcolhpc.com

lauren.haase@mineralstech.com

Principal Display Panel - Carton Label

SKIN+PHARMACY

ADVANCED
ACNE THERAPY

CLARIFYING
DAILY CLEANSER
with Polytrap® Technology

Maximum Strength 2% Salicylic Acid

- removes excess skin oils
- unclogs pores
- oil-free formula

DERMATOLOGIST TESTED

exclusively at
CVS/pharmacy

5 FL OZ (148 mL)